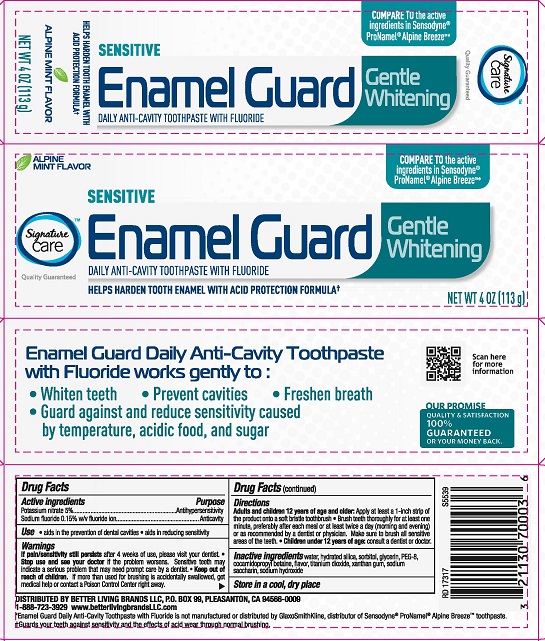 DRUG LABEL: Signature Care Enamel Guard Sensitive
NDC: 21130-350 | Form: PASTE, DENTIFRICE
Manufacturer: Safeway
Category: otc | Type: HUMAN OTC DRUG LABEL
Date: 20251114

ACTIVE INGREDIENTS: SODIUM FLUORIDE 0.15 g/100 g; POTASSIUM NITRATE 5 g/100 g
INACTIVE INGREDIENTS: GLYCERIN; WATER; SACCHARIN SODIUM; SORBITOL; POLYETHYLENE GLYCOL, UNSPECIFIED; TITANIUM DIOXIDE; SODIUM HYDROXIDE; XANTHAN GUM; HYDRATED SILICA; COCAMIDOPROPYL BETAINE

5820287 Signature Care Enamel Guard Sensitive Gentle Whitening

Drug Facts

Active ingredients

Potassium nitrate 5%

Sodium fluoride 0.15% w/v fluoride ion

Purpose

Antihypersensitivity

Anticavity

Uses

- aids in the prevention of dental cavities
- aids in reducing sensitivity

Warnings

WHEN USING

If pain/sensitivity still persists after 4 weeks of use, please visit your dentist.

Stop use and ask a dentist if the problem persists or worsens. Sensitive teeth may indicate a serious problem that may need prompt care by a dentist.

Keep out of reach of children. If more than used for brushing is accidentally swallowed, get medical help or contact a Poison Control Center right away.

Directions

Adults and children 12 years of age and older: Apply at least a 1-inch strip of the product onto a soft bristle toothbrush.

- Brush teeth thoroughly for at least one minute, preferably after each meal or at least twice a day (morning and evening) or as recommended by a dentist or physican. Make sure to brush all sensitive areas of the teeth
- Children under 12 years of age: consult a dentist or a doctor

INACTIVE INGREDIENT

Inactive ingredients water, hydrated silica, sorbitol,glycerin, PEG-8, cocamidopropyl betaine, flavor, titanium dioxide, xanthan gum, sodium saccharin, sodium hydroxide

STORAGE AND HANDLING

Store in a cool dry place

DISTRIBUTED BY BETTER LIVING BRANDS LLC, P.O. BOX 99, PLEASANTON, CA 94566-0009

1-888-723-3929 www.betterlivingbrandsLLC.com

PACKAGE LABEL

ALPINE MINT FLAVOR

Signature Care™ Enamel Guard

Gentle Whitening

DAILY ANTICAVITY TOOTHPASTE WITH FLUORIDE

HELPS HARDEN TOOTH ENAMEL WITH ACID PROTECTION FORMULA

NET WT 4 OZ (113 g)